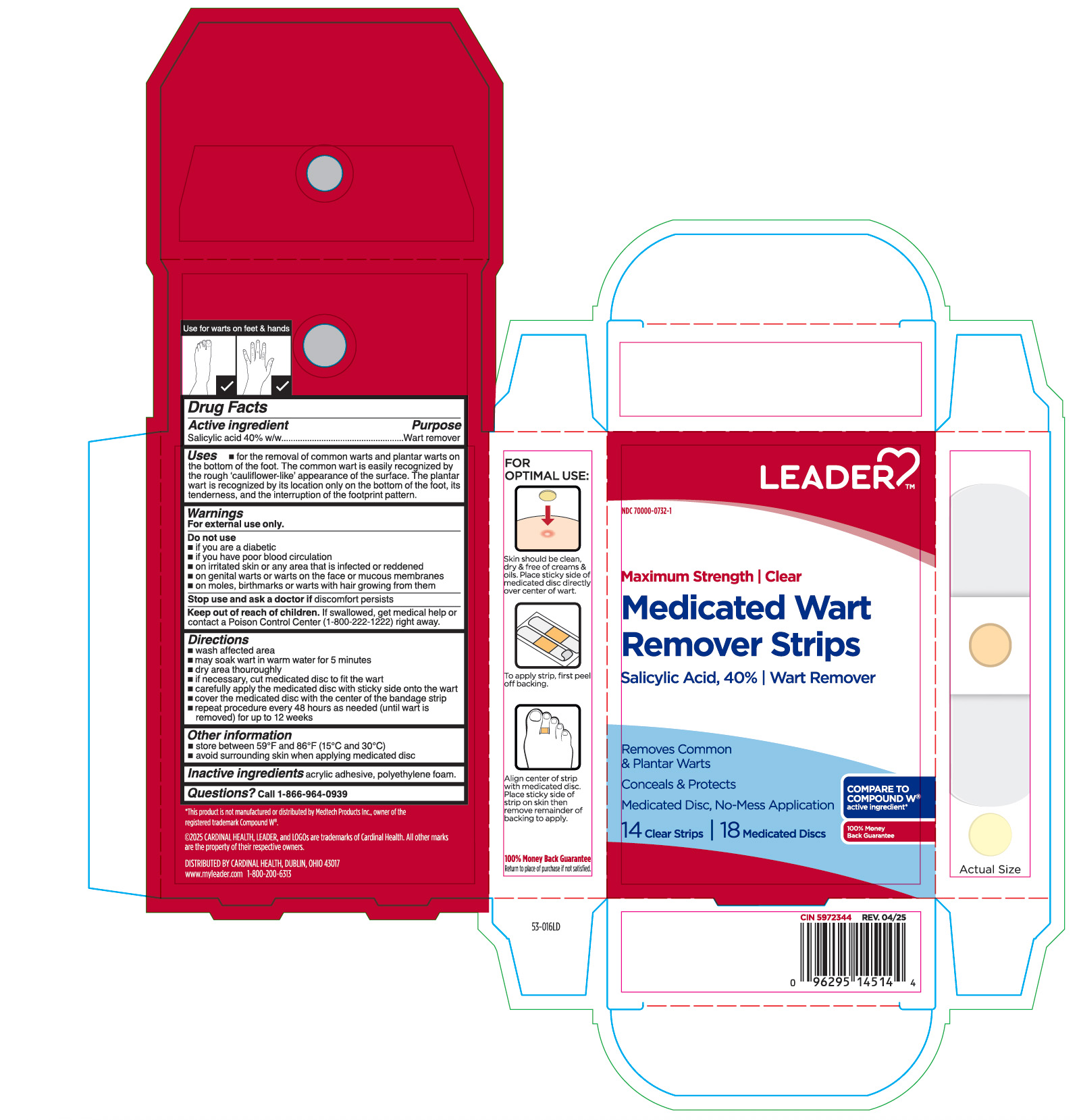 DRUG LABEL: Medicated Wart Remover Strips
NDC: 70000-0732 | Form: PLASTER
Manufacturer: CARDINAL HEALTH 110, LLC. DBA LEADER
Category: otc | Type: HUMAN OTC DRUG LABEL
Date: 20251231

ACTIVE INGREDIENTS: SALICYLIC ACID 400 mg/1 g
INACTIVE INGREDIENTS: HIGH DENSITY POLYETHYLENE

Leader Medicated Wart Remover Strips

Active ingredient

Salicylic acid 40% w/w

Purpose

Wart remover

Use

- for the removal of common warts and plantar warts on the bottom of the foot. The common wart is easily recognized by the rough 'cauliflower-like' appearance of the surface. The plantar wart is recongized by its location only on the bottom of the foot, its tenderness, and the interruption of the footprint pattern.

Warnings

For external use only.

Do not use

- if you are a diabetic
- if you have poor blood circulation
- on irritated skin or any area that is infected or reddened
- on genital warts or warts on the face or mucous membranes
- on moles, birthmarks or warts with hair growing from them

Stop use and ask a doctor if

discomfort persists

Keep out of reach of children.

If swallowed, get medical help or contact a Poison Control Center (1-800-222-1222) right away.

Directions

- wash affected area.
- may soak corn in warm water for 5 minutes.
- dry area thouroughly
- if necessary, cut medicated disc to fit the wart.
- carefully apply the medicated with sticky side onto the wart.
- cover the medicated disc with the center of the bandage strip.
- repeat procedure every 48 hours as needed (until wart is removed) for up to 12 weeks.

Other information

- store between 59°F and 86°F (15°C and 30°C)
- avoid surrounding skin when applying medicated disc

Inactive ingredients

acrylic adhesive, polyethylene foam.

Questions?

Call 1-866-964-0939

Principal Display Panel

LEADER

Maximum Strength | Clear

Medicated Wart

Remover Strips

Salicylic Acid, 40% | Wart Remover

Removes Common

& Plantar Warts

Conceals & Protects

Medicated Discs, No-Mess Application

14 Clear Strips | 18 Medicated Discs